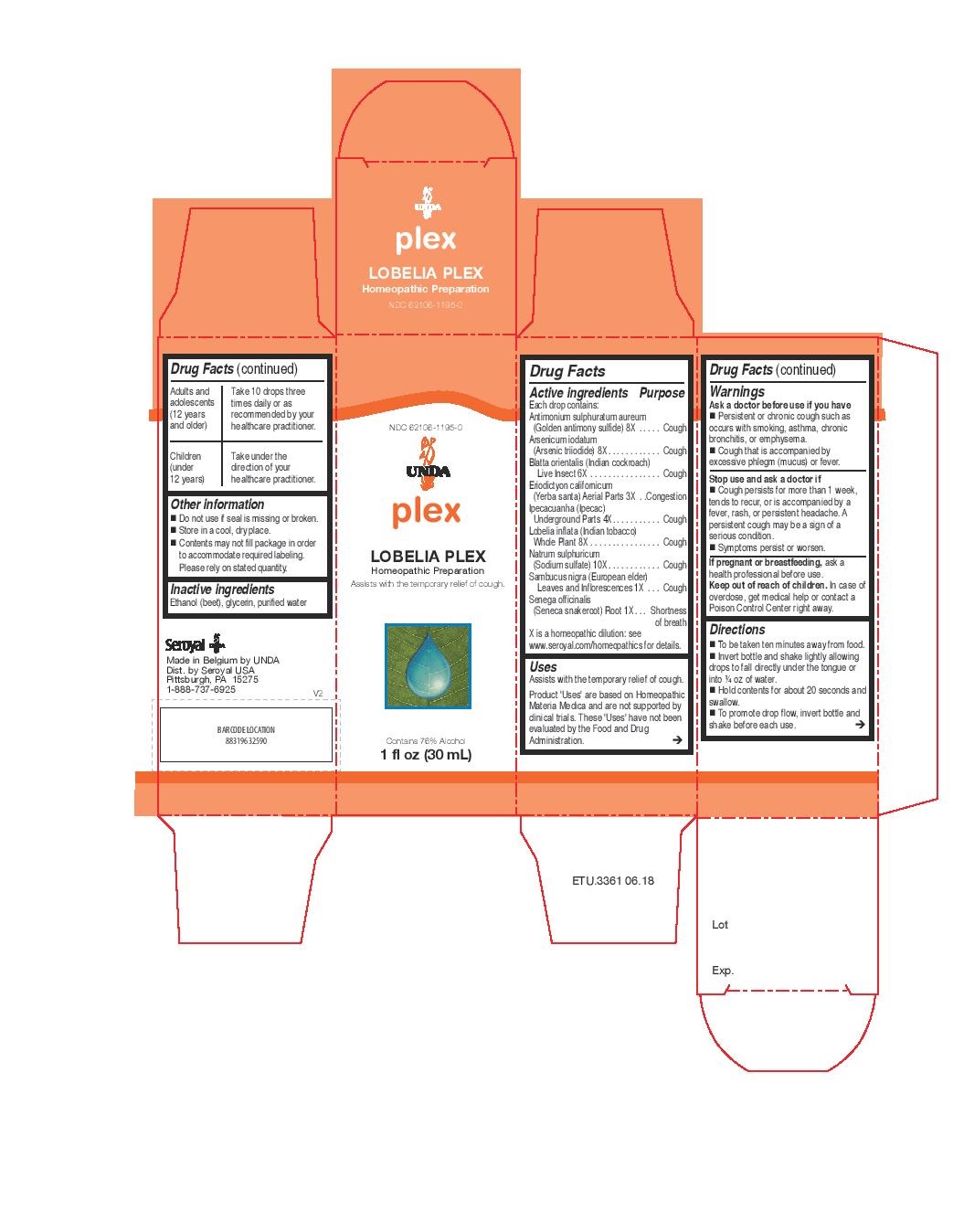 DRUG LABEL: LOBELIA PLEX
NDC: 62106-1195 | Form: LIQUID
Manufacturer: Seroyal USA
Category: homeopathic | Type: HUMAN OTC DRUG LABEL
Date: 20221109

ACTIVE INGREDIENTS: BLATTA ORIENTALIS 6 [hp_X]/30 mL; ANTIMONY PENTASULFIDE 8 [hp_X]/30 mL; ARSENIC TRIIODIDE 8 [hp_X]/30 mL; ERIODICTYON CALIFORNICUM LEAF 3 [hp_X]/30 mL; IPECAC 4 [hp_X]/30 mL; LOBELIA INFLATA 8 [hp_X]/30 mL; SODIUM SULFATE 10 [hp_X]/30 mL; SAMBUCUS NIGRA FLOWERING TOP 1 [hp_X]/30 mL; POLYGALA SENEGA ROOT 1 [hp_X]/30 mL
INACTIVE INGREDIENTS: GLYCERIN; ALCOHOL; WATER

LOBELIA PLEX

Active ingredients
Each drop contains:
Antimonium sulphuratum aureum (Golden antimony sulfide) 8X
Arsenicum iodatum (Arsenic triiodide) 8X
Blatta orientalis (Indian cockroach) Live Insect 6X
Eriodictyon californicum (Yerba santa) Aerial Parts 3X
Ipecacuanha (Ipecac) Underground Parts 4X
Lobelia inflata (Indian tobacco) Whole Plant 8X
Natrum sulphuricum (Sodium sulfate) 10X
Sambucus nigra (European elder) Leaves and Inflorescences 1X
Senega officinalis (Seneca snakeroot) Root 1X

Uses

Assists with the temporary relief of cough.

Warnings

Ask a doctor before use if you have

Persistent or chronic cough such as occurs with smoking, asthma, chronic bronchitis, or emphysema.

Cough that is accompanied by excessive phlegm (mucus) or fever.

Stop use and ask a doctor if

Cough persists for more than 1 week, tends to recur, or is accompanied by a fever, rash, or persistent headache. A persistent cough may be a sign of a serious condition.

Symptoms persist or worsen.

If pregnant or breastfeeding, ask a health professional before use.
Keep out of reach of children. In case of overdose, get medical help or contact a Poison Control Center right away.

Ask a doctor before use if you have

Persistent or chronic cough such as occurs with smoking, asthma, chronic bronchitis, or emphysema.

Cough that is accompanied by excessive phlegm (mucus) or fever.

Stop use and ask a doctor if

Cough persists for more than 1 week, tends to recur, or is accompanied by a fever, rash, or persistent headache. A persistent cough may be a sign of a serious condition.

Symptoms persist or worsen.

PREGNANCY OR BREAST FEEDING

If pregnant or breastfeeding, ask a health professional before use.

Keep out of reach of children.

OVERDOSAGE

In case of overdose, get medical help or contact a Poison Control Center right away.

Inactive ingredients
Ethanol (beet), glycerin, purified water

Other information
Do not use if seal is missing or broken.
Store in a cool, dry place.

Contents may not fill package in order to accommodate required labeling. Please rely on stated quantity.

Directions
To be taken ten minutes away from food.
Invert bottle and shake lightly allowing drops to fall directly under the tongue or into ¼ oz of water.
Hold contents for about 20 seconds and swallow.
To promote drop flow, invert bottle and shake before each use.

Adults and adolescents (12 years and older)

Take 10 drops three times daily or as recommended by your healthcare practitioner.

Children (under 12 years)

Take under the direction of your healthcare practitioner.

Uses

Assists with the temporary relief of cough.

Directions
To be taken ten minutes away from food.
Invert bottle and shake lightly allowing drops to fall directly under the tongue or into ¼ oz of water.
Hold contents for about 20 seconds and swallow.
To promote drop flow, invert bottle and shake before each use.

Adults and adolescents (12 years and older)

Take 10 drops three times daily or as recommended by your healthcare practitioner.

Children (under 12 years)

Take under the direction of your healthcare practitioner.

PACKAGE LABEL

NDC 62106-1195-0

UNDA

plex

LOBELIA PLEX

Homeopathic Preparation

Assists with the temporary relief of cough.

Contains 76% Alcohol
1 fl oz (30 mL)